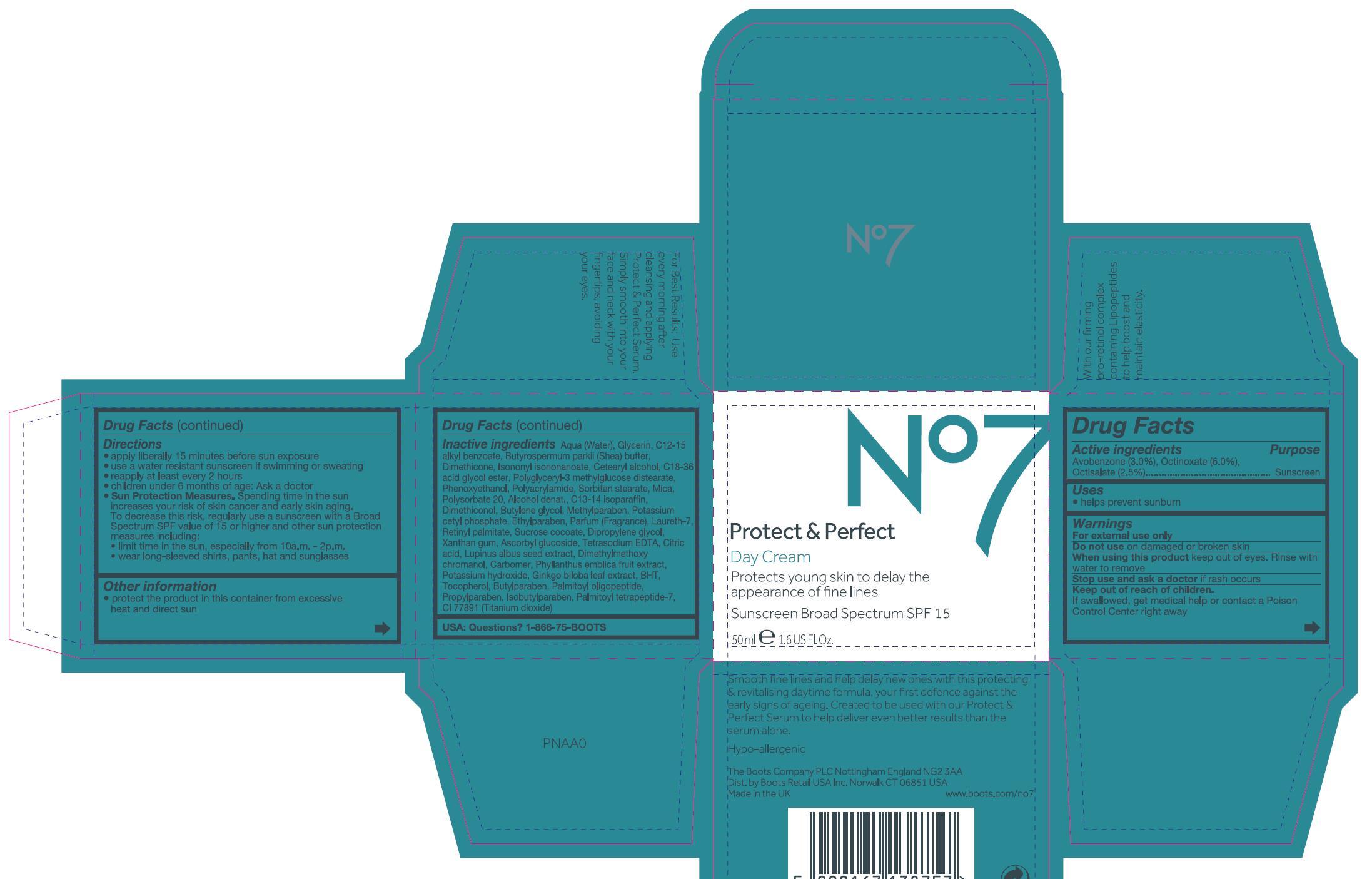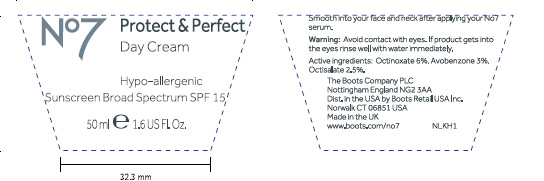 DRUG LABEL: No7 Protect and Perfect Day Sunscreen Broad Spectrum SPF 15
NDC: 68472-109 | Form: CREAM
Manufacturer: Boots Retail USA Inc
Category: otc | Type: HUMAN OTC DRUG LABEL
Date: 20120601

ACTIVE INGREDIENTS: Avobenzone 1.5 mL/50 mL; Octinoxate 3 mL/50 mL; Octisalate 1.25 mL/50 mL
INACTIVE INGREDIENTS: Water; Glycerin; ALKYL (C12-15) BENZOATE; SHEA BUTTER; Dimethicone; ISONONYL ISONONANOATE; CETOSTEARYL ALCOHOL; PHENOXYETHANOL; SORBITAN MONOSTEARATE; mica; POLYSORBATE 20; ALCOHOL; C13-14 ISOPARAFFIN; BUTYLENE GLYCOL; METHYLPARABEN; POTASSIUM CETYL PHOSPHATE; ETHYLPARABEN; LAURETH-7; VITAMIN A PALMITATE; SUCROSE COCOATE; DIPROPYLENE GLYCOL; XANTHAN GUM; ASCORBYL GLUCOSIDE; EDETATE SODIUM; CITRIC ACID MONOHYDRATE; LUPINUS ALBUS SEED; PHYLLANTHUS EMBLICA FRUIT; POTASSIUM HYDROXIDE; GINKGO; BUTYLATED HYDROXYTOLUENE; TOCOPHEROL; BUTYLPARABEN; PALMITOYL OLIGOPEPTIDE; PROPYLPARABEN; ISOBUTYLPARABEN; PALMITOYL TETRAPEPTIDE-7; TITANIUM DIOXIDE

Carton and jar labelling

ACTIVE INGREDIENT

Active Ingredients Avobenzone (3.0%), Octinoxate (6.0%), Octisalate (2.5%)

Purpose Sunscreen

PURPOSE

Uses helps prevent sunburn

Warnings

For external use only

Do not use on damaged or broken skin

When using this product keep out if eyes. Rinse with water to remove.

Stop use and ask a doctor if rash occurs.

Keep out of reach of children. If swallowed get medical help or contact a poison control center right away.

INDICATIONS AND USAGE

Directons

Apply liberally 15 minutes before sun exposure

Use a water resistant sunscreen if swimming or sweating

Reapply at least every 2 hours

Chidren under 6 months of age: Ask a doctor

Sun Protection Measures

Spending time in the sun increases your risk of skin cancer and early skin aging. To decrease this risk, regularly use a sunscreen with a broad spectrum SPF value of 15 or higher and other sun protection measures including:

limit time in the sun, especially from 10a,m - 2p.m

wear long-sleeved shirts, pants, hat and sunglasses

Other information

Protect the product in this container from excessive heat and direct sun

Inactive Ingredients

Aqua (water), Glycerin, C12-15 alkyl benzoate, Butyrospermum parkii (shea) butter, Dimethicone, Isononyl isonanoate, Cetearyl alcohol, C18-36 acid glycol ester, Polyglyceryl-3-methylglucose distearate, Phenoxyethanol, Polyacrylamide, Sorbitan stearate, Mica, Polysorbate 20, Alcohol denat., Methylparaben, Potassium cetyl phosphate, Ethylparaben, Parfum (fragrance), Laureth-7, Retinyl palmitate, Sucrose cocoate, Dipropylene glycol, Xanthan gum, ascorbyl glucoside, Tetrasodium EDTA, Citric acid, Lupinus albus seed extract, Dimethylmethoxy chromanol, Carbomer, Phyllanthus emblica fruit extract, Potassium hydroxide, Ginkgo biloba leaf extract, BHT, Tocopherol, Butylparaben, Palmitoyl oligopeptide, Propylparaben, Isobutylparaben, Palmitoyl tetrapeptide-7, CI 77891 (Titanium dioxide)

USA: Questions? 1-866-75-BOOTS

DESCRIPTION

Smooth fine lines and help delay new ones with this protecting and revitalising daytime formula, your first defence against the early signs of ageing. Created to be used with our protect and pefect serum to help deliver even better results that the serum alone.

PATIENT COUNSELING INFORMATION

Hypoallergenic
The Boots company PLC Nottingham England NG2 3AA
Dist. by Boots Retail USA Inc. Norwalk CT 06851 USA
Made in the UK
www.Boots.com/no7

DESCRIPTION

For best results use every morning after cleansing and applying protect and perfect serum. Simply smooth into our face and neck with your fingertips, avoiding your eyes.

With our firming pro-retinol complex containing lipopeptides to help boost and maintain elasticity.

ACTIVE INGREDIENT

JAR TEXT

Active ingredients: Octinoxate 6%, Avobenzone 3%, Octisalate 2.5%

WARNINGS

JAR TEXT

Warning: Avoid contact with eyes. If product gets into the eyes rinse well with water immediately.

INDICATIONS AND USAGE

JAR TEXT

Smooth into your face and neck after applying your No7 serum.

PATIENT COUNSELING INFORMATION

JAR TEXT

The Boots Company PLC Nottingham England NG2 3AA
Dist. in the USA by Boots Retail USA Inc. Norwalk CT 06851 USA
Made in the UK
www.Boots.com/no7

PACKAGE LABEL

No7 Protect and Perfect

Day Cream

Protects young skin to delay the appearance of fine lines

Sunscreen broad spectrum SPF 15

50ml 1.6US Fl.Oz

P and P Day Cream carton.jpg

PACKAGE LABEL

JAR TEXT

No7 Protect and Perfect Day Cream

Hypo-allergenic

Sunscreen Broad Spectrum SPF 15

50ml 1.6 US Fl.Oz

P and P Day Cream jar.jpg